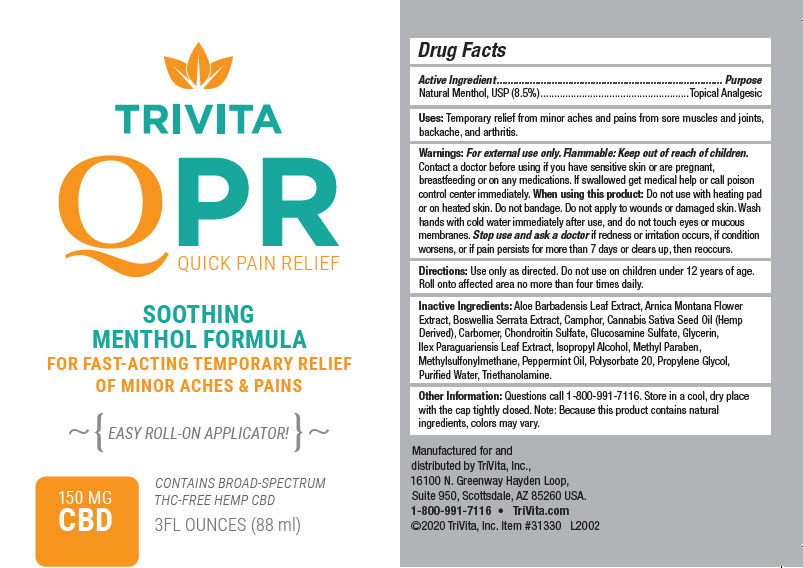 DRUG LABEL: TRIVITA QPR
NDC: 76571-313 | Form: GEL
Manufacturer: TriVita, Inc.
Category: otc | Type: HUMAN OTC DRUG LABEL
Date: 20221222

ACTIVE INGREDIENTS: MENTHOL, UNSPECIFIED FORM 8.5 g/100 mL
INACTIVE INGREDIENTS: Aloe Vera Leaf; Arnica Montana Flower; Indian Frankincense; CANNABIS SATIVA SEED OIL; Carbomer Homopolymer, Unspecified Type; Glucosamine Sulfate; Glycerin; Ilex Paraguariensis Leaf; Isopropyl Alcohol; MethylParaben; Dimethyl Sulfone; Peppermint Oil; Polysorbate 20; Propylene Glycol; Water; Trolamine

TRIVITA QPR

Drug Facts

Active Ingredient

Natural Menthol, USP (8.5%)

Purpose

Topical Analgesic

Uses

Temporary relief from minor aches and pains from sore muscles and joints, backache, and arthritis.

Warnings

For external use only.

Flammable: Keep out of reach of children.

Contact a doctor before using if you have sensitive skin or are pregnant, breastfeeding or on any medications. If swallowed get medical help or call poison control center immediately.

When using this product

Do not use with heating pad or on heated skin. Do not bandage. Do not apply to wounds or damaged skin. Wash hands with cold water immediately after use, and do not touch eyes or mucous membranes.

Stop use and ask a doctor if redness or irritation occurs, if condition worsens, or if pain persists for more than 7 days or clears up, then reoccurs.

Directions

Use only as directed. Do not use on children under 12 years of age. Roll onto affected area no more than four times daily.

Inactive Ingredients

Aloe Barbadensis Leaf Extract, Arnica Montana Flower Extract, Boswellia Serrata Extract, Camphor, Cannabis Sativa Seed Oil (Hemp Derived), Carbomer, Chondroitin Sulfate, Glucosamine Sulfate, Glycerin, Ilex Paraguariensis Leaf Extract, Isopropyl Alcohol, Methyl Paraben, Methylsulfonylmethane, Peppermint Oil, Polysorbate 20, Propylene Glycol, Purified Water, Triethanolamine.

Other Information

Questions call 1-800-991-7116. Store in a cool, dry place with the cap tightly closed. Note: Because this product contains natural ingredients, colors may vary.

distributed by TriVita, Inc.,
16100 N. Greenway Hayden Loop,
Suite 950, Scottsdale, AZ 85260 USA.

PRINCIPAL DISPLAY PANEL - 88 ml Bottle Label

TRIVITA
QPR
QUICK PAIN RELIEF

SOOTHING
MENTHOL FORMULA
FOR FAST-ACTING TEMPORARY RELIEF
OF MINOR ACHES & PAINS

~{ EASY ROLL-ON APPLICATOR!}~

150 MG
CBD

CONTAINS BROAD-SPECTRUM
THC-FREE HEMP CBD

3FL OUNCES (88 ml)